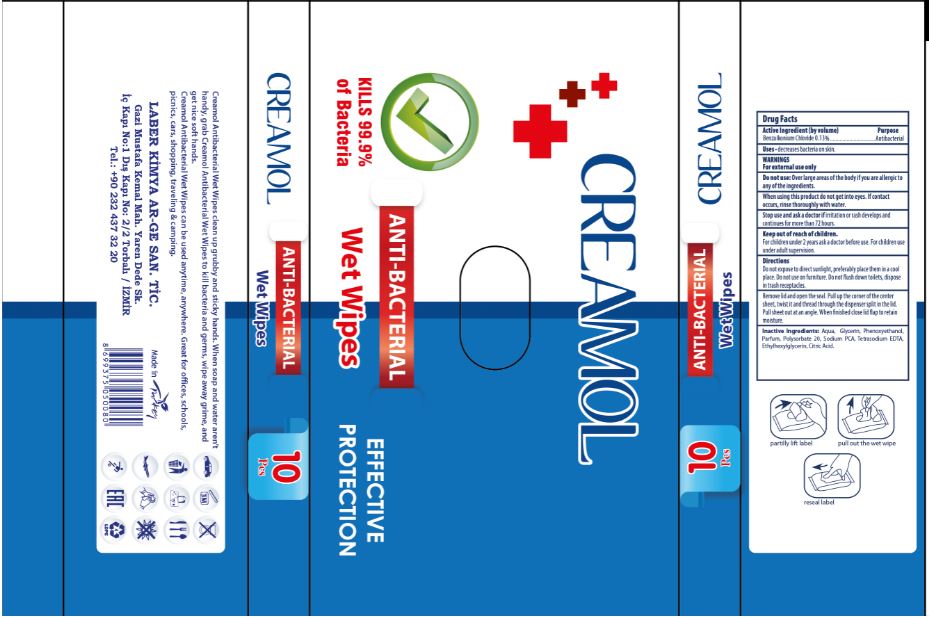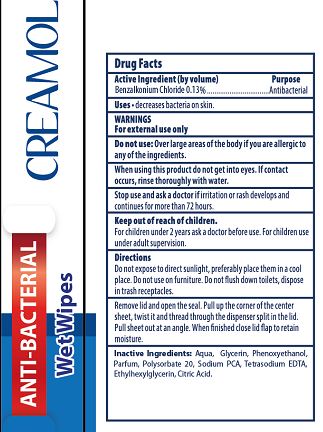 DRUG LABEL: ANTIBACTERIAL WET WIPES
NDC: 77892-0002 | Form: SWAB
Manufacturer: LABER KIMYA AR-GE SANAYI TICARET - LEVENT KAHRIMAN
Category: otc | Type: HUMAN OTC DRUG LABEL
Date: 20200608

ACTIVE INGREDIENTS: BENZALKONIUM CHLORIDE 0.13 g/100 g
INACTIVE INGREDIENTS: POLYSORBATE 20; TRIMETHYLENEDIAMINETETRAACETIC ACID; GLYCERIN; ETHYLHEXYLGLYCERIN; SODIUM PYRROLIDONE CARBOXYLATE; WATER; ANHYDROUS CITRIC ACID

PURPOSE

Antibacterial

WARNINGS

For external use only.Keep out of the eyes. In case of eye contact, rinse with water.If irritation develps discontinue use and consult a doctor if irritation persists more than 72 hours. If swallowed, seek medical attention or contact a Poison Control Center.

INACTIVE INGREDIENT

Aqua, Glycerin, Phenoxyethanol, Parfum, Polysorbate 20, Sodium PCA, Tetrasodium EDTA, Ethylhexylglycerin, Citric Acid

ACTIVE INGREDIENT

Benzalkonium chloride 0.13%

INDICATIONS AND USAGE

decreases bacteria on skin. recommended for repeated use

KEEP OUT OF REACH OF CHILDREN

Keep out of the reach of children, except with adult supervision.

DOSAGE AND ADMINISTRATION

Take wipe and rub thoroughly over all surfaces of both hands.Rrub hands together briskly to dry·dispose of wipe. For children under 2 years ask a doctor before use.